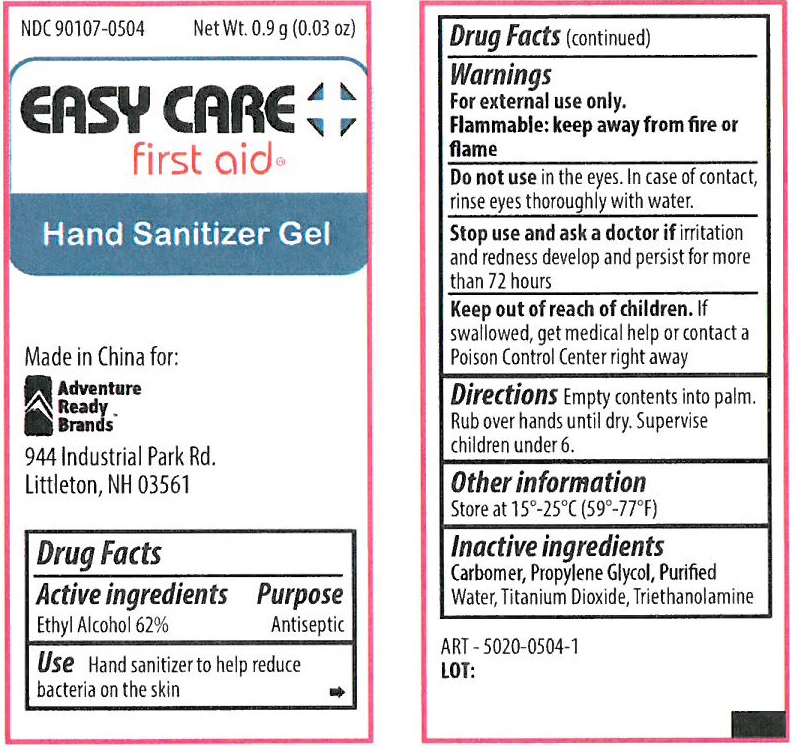 DRUG LABEL: Easy Care Hand Sanitizer
NDC: 50814-066 | Form: GEL
Manufacturer: GFA Production (Xiamen) Co., Ltd.
Category: otc | Type: HUMAN OTC DRUG LABEL
Date: 20250127

ACTIVE INGREDIENTS: ALCOHOL 62 g/100 g
INACTIVE INGREDIENTS: CARBOMER HOMOPOLYMER, UNSPECIFIED TYPE; PROPYLENE GLYCOL; WATER; TITANIUM DIOXIDE; TROLAMINE

Easy Care Hand Sanitizer Gel

Active ingredients

Ethyl Alcohol 62%

Purpose

Antiseptic

Use

Hand sanitizer to help reduce bacteria on the skin

Warnings

For external use only.

Flammable:keep away from fire or flame

Do not use

in the eyes. In case of contact, rinse eyes thoroughly with water.

Stop use and ask a doctor if

irritation and redness develop and persist for more than 72 hours

Keep out of reach of children.

If swallowed, get medical help or contact a Poison Control Center right away

Directions

Empty contents into palm. Rub over hands until dry. Supervise children under 6.

Other information

Store at 15°-25°C (59°-77°F)

Inactive ingredients

Carbomer, Propylene Glycol, Purified Water, Titanium Dioxide, Triethanolamine